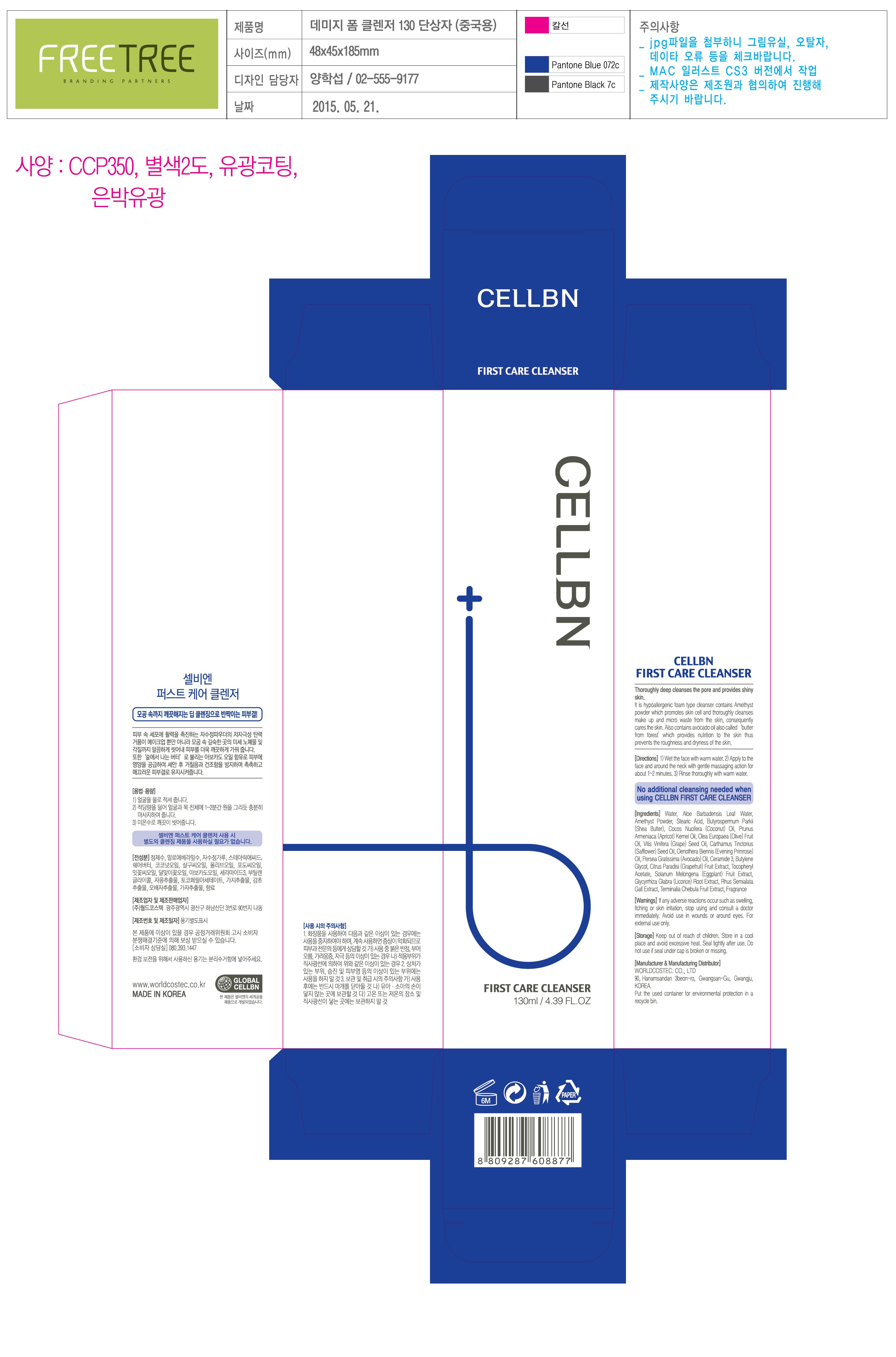 DRUG LABEL: CELLBN FIRST CARE CLEANSER
NDC: 71450-0006 | Form: CREAM
Manufacturer: WORLDCOSTEC.CO.,LTD
Category: otc | Type: HUMAN OTC DRUG LABEL
Date: 20170529

ACTIVE INGREDIENTS: STEARIC ACID 16 g/100 mL
INACTIVE INGREDIENTS: WATER; BUTYLENE GLYCOL

ACTIVE INGREDIENT

Stearic Acid

INACTIVE INGREDIENT

Water, Butylene Glycol, Etc

PURPOSE

Skin Protectant - Cleasing

Keep out of reach of the children

INDICATIONS AND USAGE

1. Wet the face with warm water.
2. Apply to the face and around the neck with gently massaging action for abount 1~2 minutes.
3. Rinse thoroughly with warm water.

WARNINGS

1. If the following symptoms occur after product use, stop using the product immediately and consult a dermatologist (continuous use can exacerbate the symptoms).
1) Occurrence of red spots, swelling, itchiness, and other skin irritation
2) If the symptoms above occur after the application area is exposed to direct sunlight

2. Do not use on open wounds, eczema, and other skin irritations

3. Precaution for Storage and Handling
1) Close the lid after use
2) Keep out of reach of infants and children
3) Do not to store in a place with high/low temperature and exposed to direct sunlight

4. Use as avoiding eye areas.

DOSAGE AND ADMINISTRATION

for external use only